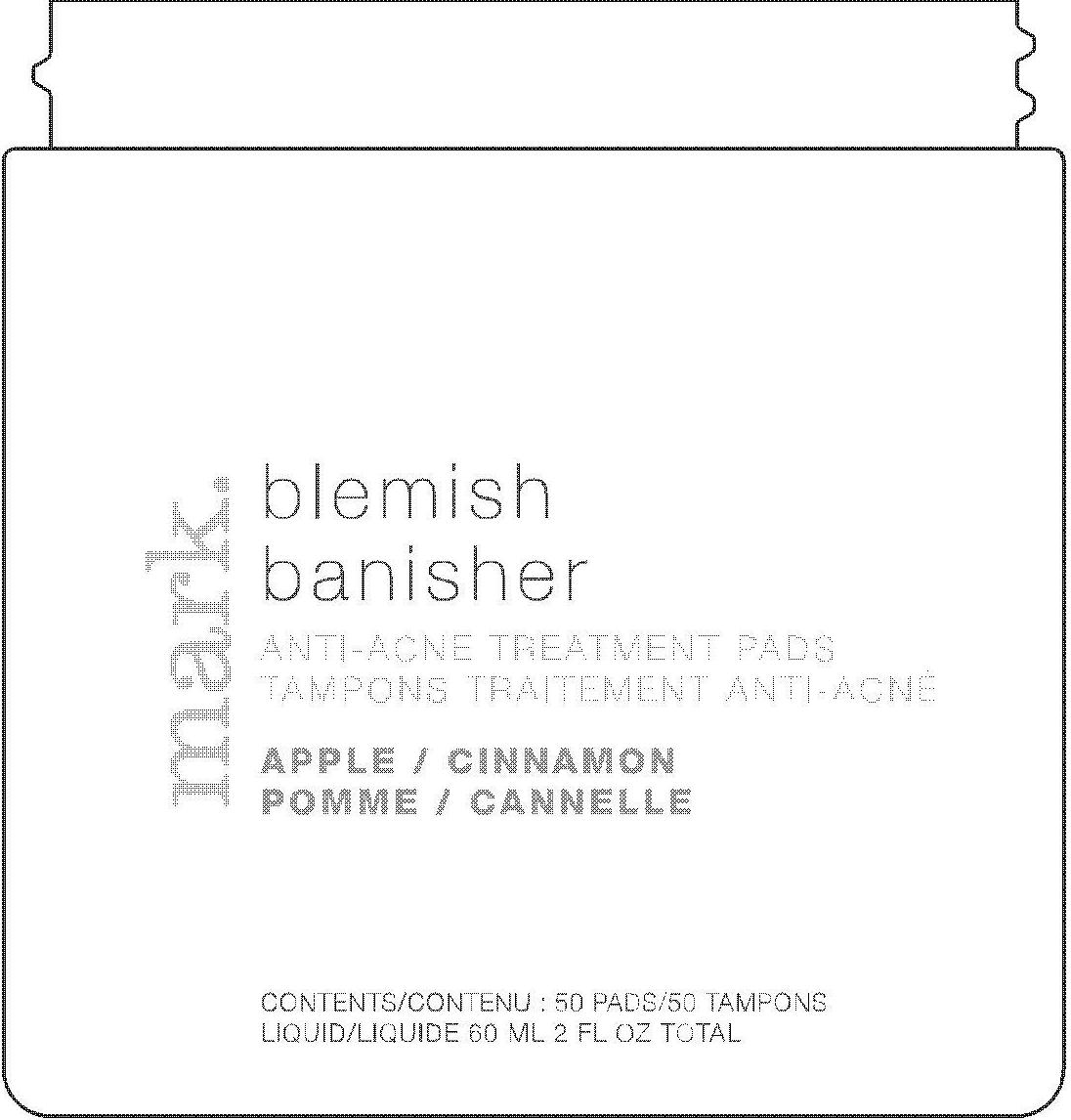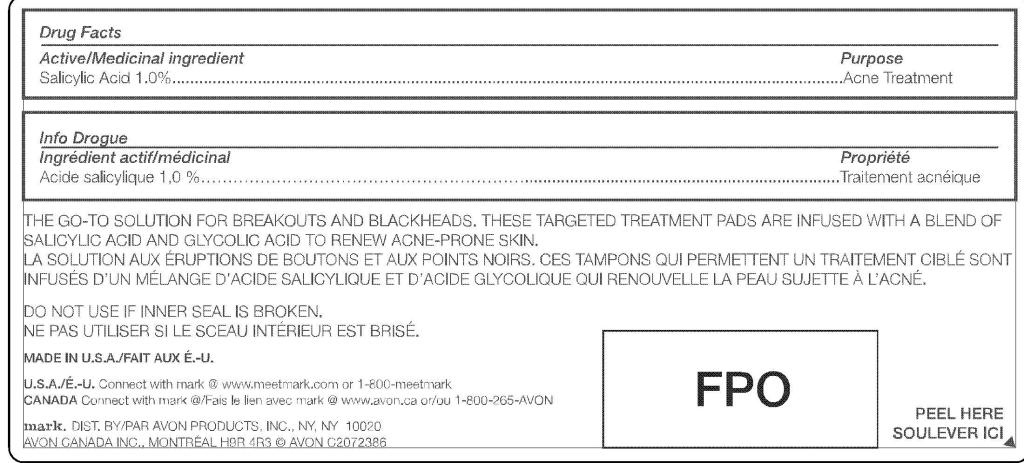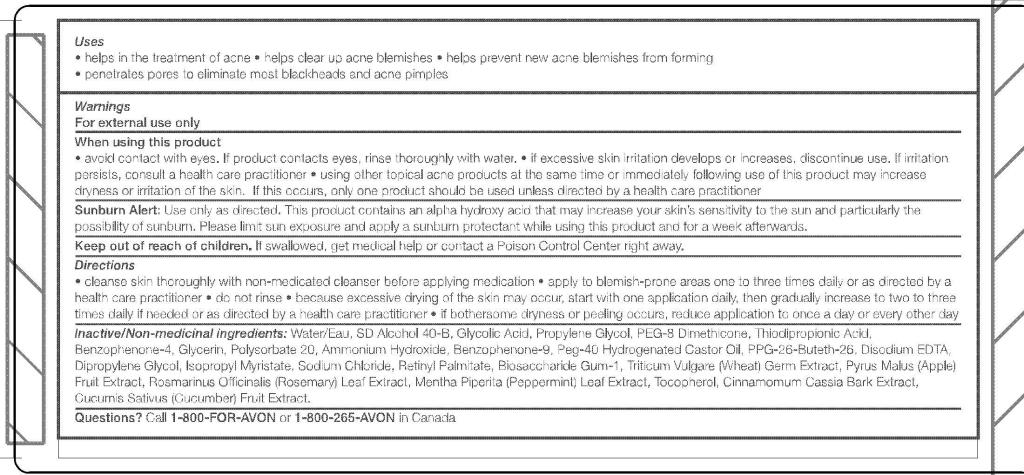 DRUG LABEL: MARK. BLEMISH BANISHER
NDC: 10096-0194 | Form: CLOTH
Manufacturer: Avon Products, Inc. 
Category: otc | Type: HUMAN OTC DRUG LABEL
Date: 20091229

ACTIVE INGREDIENTS: SALICYLIC ACID .6 mL/60 mL
INACTIVE INGREDIENTS: GLYCOLIC ACID; PROPYLENE GLYCOL; GLYCERIN; POLYSORBATE 20; DIPROPYLENE GLYCOL; ISOPROPYL MYRISTATE; SODIUM CHLORIDE

DRUG FACTS

Active ingredient Purpose
Salicylic Acid 1.00%....................................Acne Treatment

Uses

- helps in the treatment of acne
- helps clear up acne blemishes
- helps prevent new acne blemishes from forming
- penetrates pores to eliminate most blackheads and acne pimples

Warnings
For external use only

When using this product

- avoid contact with eyes. If product contacts eyes, rinse thoroughly with water.
- if excessive skin irritation develops or increases, discontinue use. If irritation persists, consult a health care practitioner
- using other topical acne products at the same time or immediately following use of this product may increase dryness or irritation of the skin. If this occurs, only one product should be used unless directed by a health care practitioner

GENERAL PRECAUTIONS

Sunburn Alert: Use only as directed. This product contains alpha hydroxy acid that may increase you skin's sensitivity to the sun and particularly the possibility of sunburn. Please limit sun exposure and apply a sunburn protectant while using this product and for a week afterwards.

This product

Keep out of reach of children. If swallowed, get medical help or contact a Poison Control Center right away.

STORAGE AND HANDLING

Flammable. Keep away from heat or flame.

Directions

- cleanse skin thoroughly with non-medicated cleanser before applying medication
- apply to blemish-prone areas one to three times daily or as directed by a health care practitioner
- do not rinse
- because excessive drying of the skin may occur, start with one application daily, then gradually increase to two to three times daily if needed or as directed by a health care practitioner
- if bothersome dryness or peeling occurs, reduce application to once a day or every other day

Inactive/Non-medicinal
ingredients
WATER/EAU
SD ALCOHOL 40-B
GLYCOLIC ACID
PROPYLENE GLYCOL
PEG-8 DIMETHICONE
THIODIPROPIONIC ACID
TRITICUM VULGARE (WHEAT) GERM EXTRACT
PYRUS MALUS (APPLE) FRUIT EXTRACT
ROSMARINUS OFFICINALIS (ROSEMARY) LEAF EXTRACT
MENTHA PIPERITA (PEPPERMINT) LEAF EXTRACT
CINNAMOMUM CASSIA BARK EXTRACT
CUCUMIS SATIVUS (CUCUMBER) FRUIT EXTRACT
TOCOPHEROL
BENZOPHENONE-4
GLYCERIN
POLYSORBATE 20
BENZOPHENONE-9
PEG-40 HYDROGENATED CASTOR OIL
PPG-26-BUTETH-26
DIPROPYLENE GLYCOL
ISOPROPYL MYRISTATE
SODIUM CHLORIDE
RETINYL PALMITATE
BIOSACCHARIDE GUM-1
AMMONIUM HYDROXIDE
DISODIUM EDTA

QUESTIONS

Questions? Call 1-800-FOR-AVON or 1-800-265-AVON in Canada.